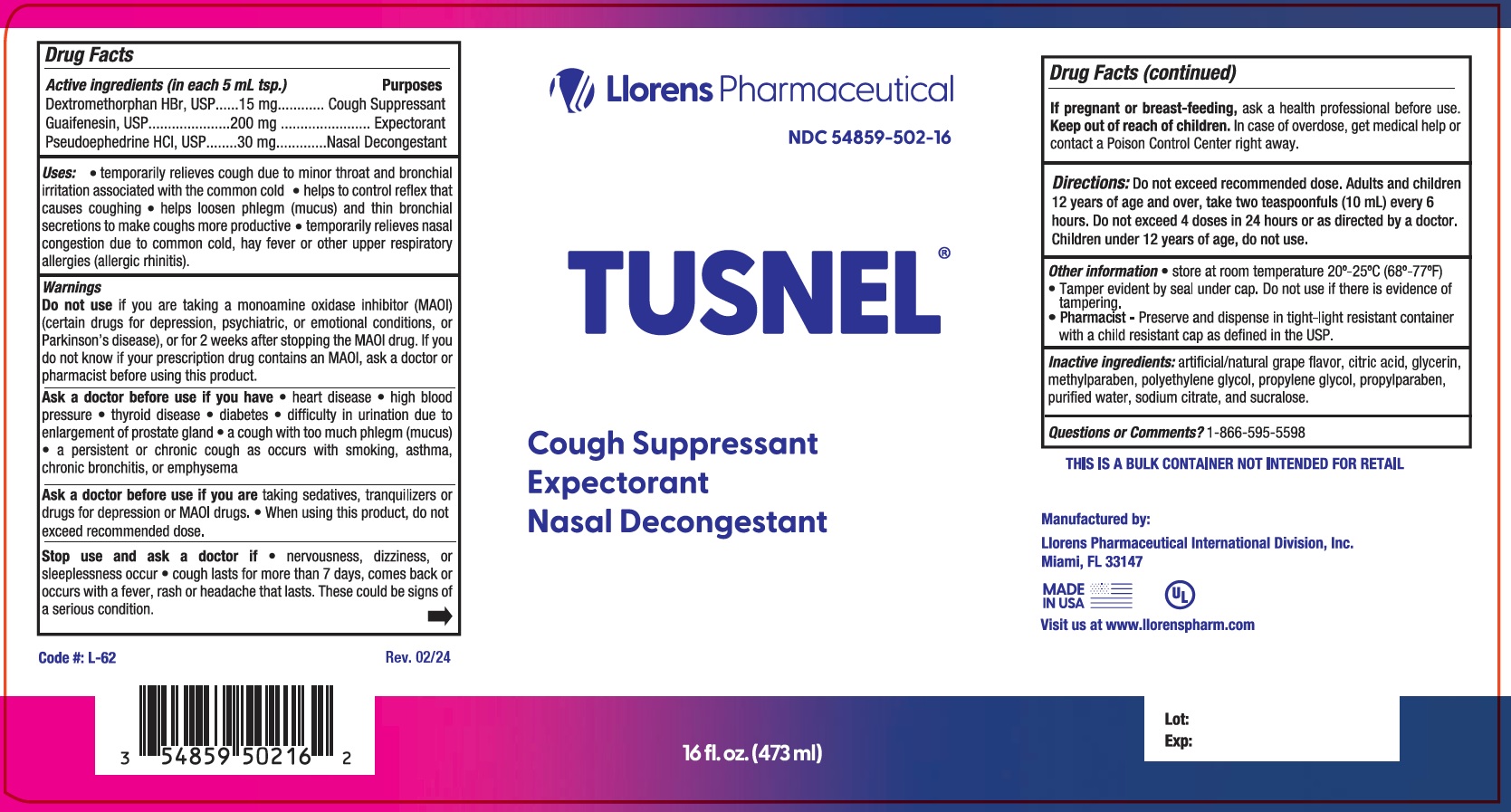 DRUG LABEL: Tusnel
NDC: 54859-502 | Form: LIQUID
Manufacturer: Llorens Pharmaceutical International Division
Category: otc | Type: HUMAN OTC DRUG LABEL
Date: 20251231

ACTIVE INGREDIENTS: DEXTROMETHORPHAN HYDROBROMIDE 15 mg/5 mL; GUAIFENESIN 200 mg/5 mL; PSEUDOEPHEDRINE HYDROCHLORIDE 30 mg/5 mL
INACTIVE INGREDIENTS: SODIUM CITRATE; SUCRALOSE; CITRIC ACID MONOHYDRATE; GLYCERIN; METHYLPARABEN; POLYETHYLENE GLYCOL, UNSPECIFIED; PROPYLENE GLYCOL; PROPYLPARABEN; WATER

Llorens- Tusnel 502

Active Ingredients(in each 5 ml tsp.) Purpose

Dextromethorphan HBr........15mg..................................................Cough Suppressant

Guaifenesin........................200mg................................................Expectorant

Pseudoephedrine HCl..........30mg..................................................Nasal Decongestant

Purpose

Cough Suppressant

Expectorant

Nasal Decongestant

Warnings
Do not useif you are now taking a prescription monoamine oxidase inhibitor (MAOI) (certain drugs for depression, psychiatric, or emotional
conditions, or Parkinson’s disease), or for 2 weeks after stopping the MAOI drug. If you do not know if your prescription drug contains an MAOI, ask a doctor or pharmacist before taking this product.

Ask a doctor before use if you have

- heart disease
- high blood pressure
- thyroid disease
- diabetes
- difficulty in urination due to enlargement of prostate gland
- a cough with too much phlegm (mucus)
- a persistent or chronic cough as occurs with smoking, asthma, chronic bronchitis, or emphysema

Ask a doctor before use if you are taking sedatives, tranquilizers or drugs for depression or MAOI drugs.

Stop use and ask a doctor if

- nervousness, dizziness, or sleeplessness occur
- cough lasts for more than 7 days, comes back or occurs with a fever, rash or headache that lasts. These could be signs of a serious condition

Keep out of reach of children.In case of overdose, get medical help or contact a Poison Control Center right away.

PREGNANCY OR BREAST FEEDING

If pregnant or breast-feeding, ask a health professional before use.

DOSAGE AND ADMINISTRATION

DirectionsDo not exceed more than 4 doses in any 24-hour period
or as directed by a doctor.

Age | Dose
Adults and children 12 years of age and over | Take 2 teaspoonfuls (10 mL) every 6 hours

Uses:

- temporarily relieves cough due to minor throat and bronchial irritation associated with the common cold
- helps control reflex that causes coughing
- helps loosen phlegm (mucus) and thin bronchial secretions to make coughs more productive
- temporarily relieves nasal congestion due to common cold, hay fever or other upper respiratory allergies (allergic rhinitis).

INACTIVE INGREDIENT

Inactive ingredients: artificial grape flavor, citric acid, glycerin, methylparaben, polyethylene glycol, propylene glycol, propylparaben, purified water, sodium citrate and sucralose.

Questions or Comments?1-866-595-5598